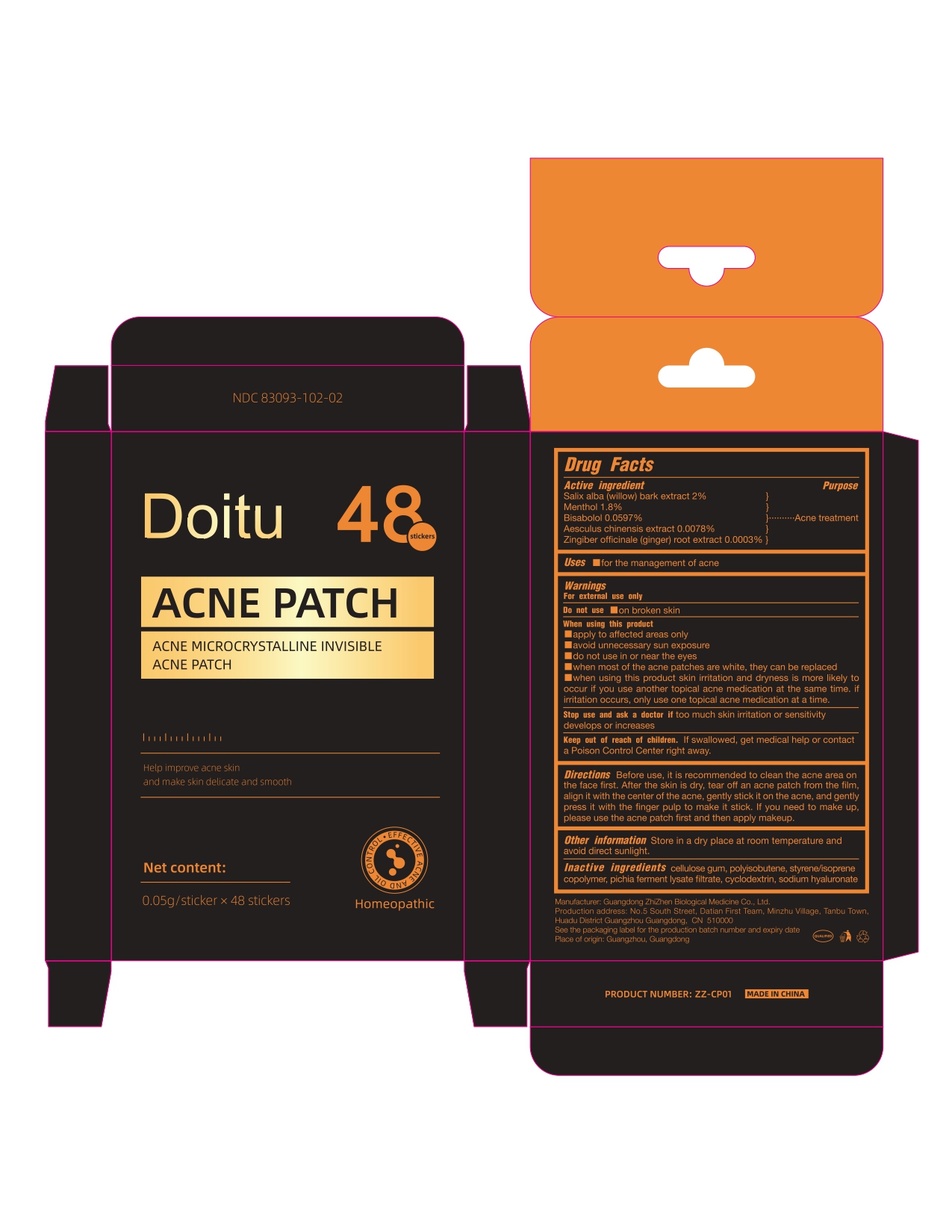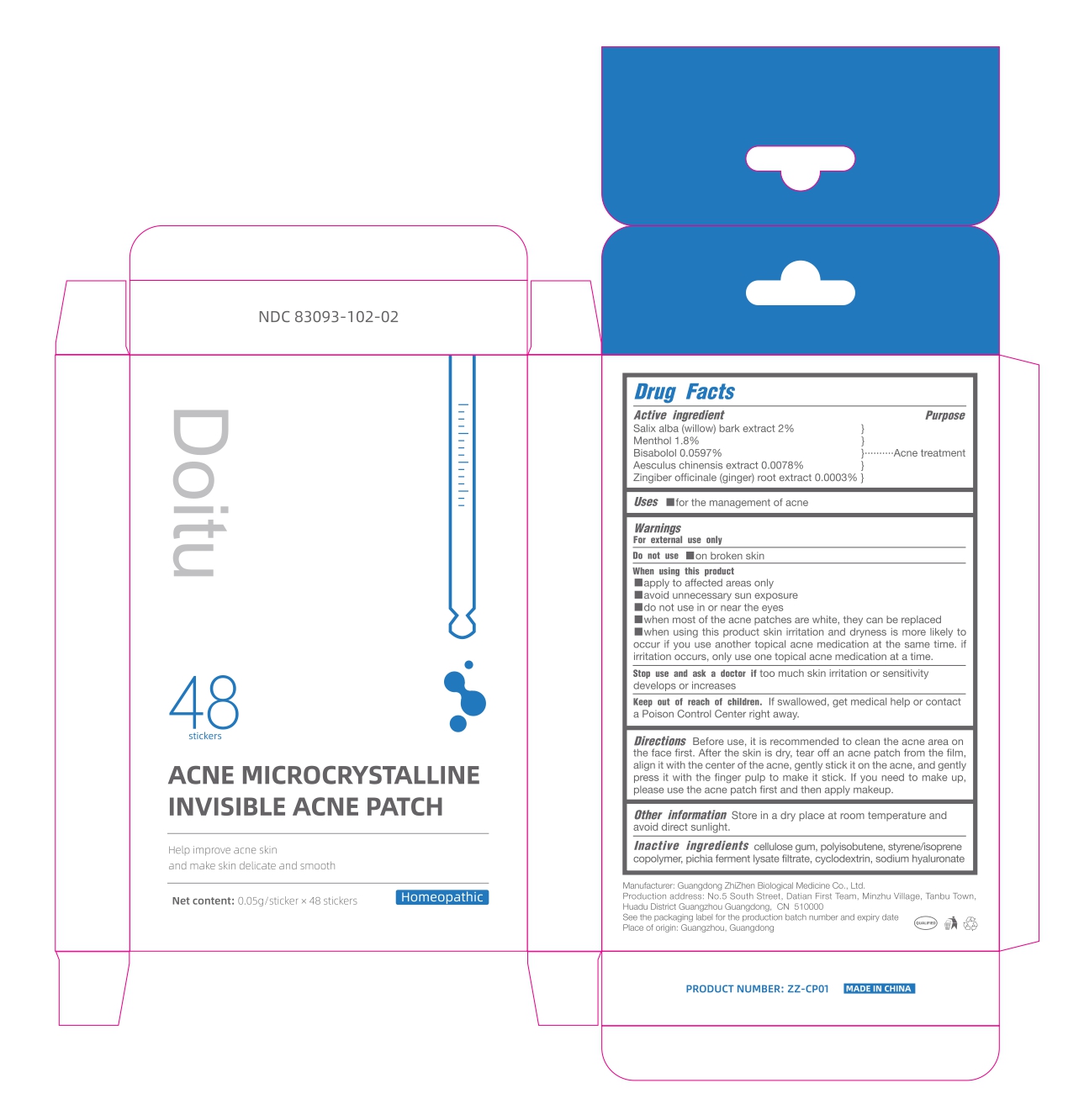 DRUG LABEL: Doitu acne microcrystalline invisible acne patch
NDC: 83093-102 | Form: PATCH
Manufacturer: Guangdong ZhiZhen Biological Medicine Co., Ltd.
Category: homeopathic | Type: HUMAN OTC DRUG LABEL
Date: 20221124

ACTIVE INGREDIENTS: GINGER 0.00015 mg/50 mg; MENTHOL 0.9 mg/50 mg; SALIX ALBA BARK 1 mg/50 mg; LEVOMENOL 0.02985 mg/50 mg; AESCULUS CHINENSIS WHOLE 0.0039 mg/50 mg
INACTIVE INGREDIENTS: POLYISOBUTYLENE (1000 MW) 18.9 mg/50 mg; HYALURONATE SODIUM 0.01 mg/50 mg; CYCLODEXTRINS 0.0561 mg/50 mg; STYRENE/ISOPRENE/STYRENE BLOCK COPOLYMER 7.0875 mg/50 mg; CARBOXYMETHYLCELLULOSE SODIUM, UNSPECIFIED FORM 21.2625 mg/50 mg; PICHIA JADINII 0.75 mg/50 mg

ACTIVE INGREDIENT

SALIX ALBA (WILLOW) BARK EXTRACT 2%
MENTHOL 1.8%
BISABOLOL 0.0597%
AESCULUS CHINENSIS EXTRACT 0.0078%
ZINGIBER OFFICINALE (GINGER) ROOT EXTRACT 0.0003%

PURPOSE

Acne treatment

WARNINGS

For external use only

WHEN USING

■Apply to affected areas only
■Avoid unnecessary sun exposure
■Do not use in or near the eyes
■When most of the acne patches are white, they can be replaced
■When using this product skin irritation and dryness is more likely to occur if you use another topical acne medication at the same time. If irritation occurs, only use one topical acne medication at a time.

Stop use and ask a doctor if too much skin irritation or sensitivity develops or increases.

Keep out of reach of children. If swallowed, get medical help or contact a Poison Control Center right away.

Directions

Before use, it is recommended to clean the acne area on the face first. After the skin is dry, tear off an acne patch from the film, align it with the center of the acne, gently stick it on the acne, and gently press it with the finger pulp to make it stick. If you need to make up, please use the acne patch first and then apply makeup.

DOSAGE AND ADMINISTRATION

Use as needed until acne subsides.

OTHER SAFETY INFORMATION

Store in a dry place at room temperature and avoid direct sunlight.

INACTIVE INGREDIENT

CELLULOSE GUM, POLYISOBUTENE, STYRENE/ISOPRENE COPOLYMER, PICHIA FERMENT LYSATE FILTRATE, CYCLODEXTRIN, SODIUM HYALURONATE